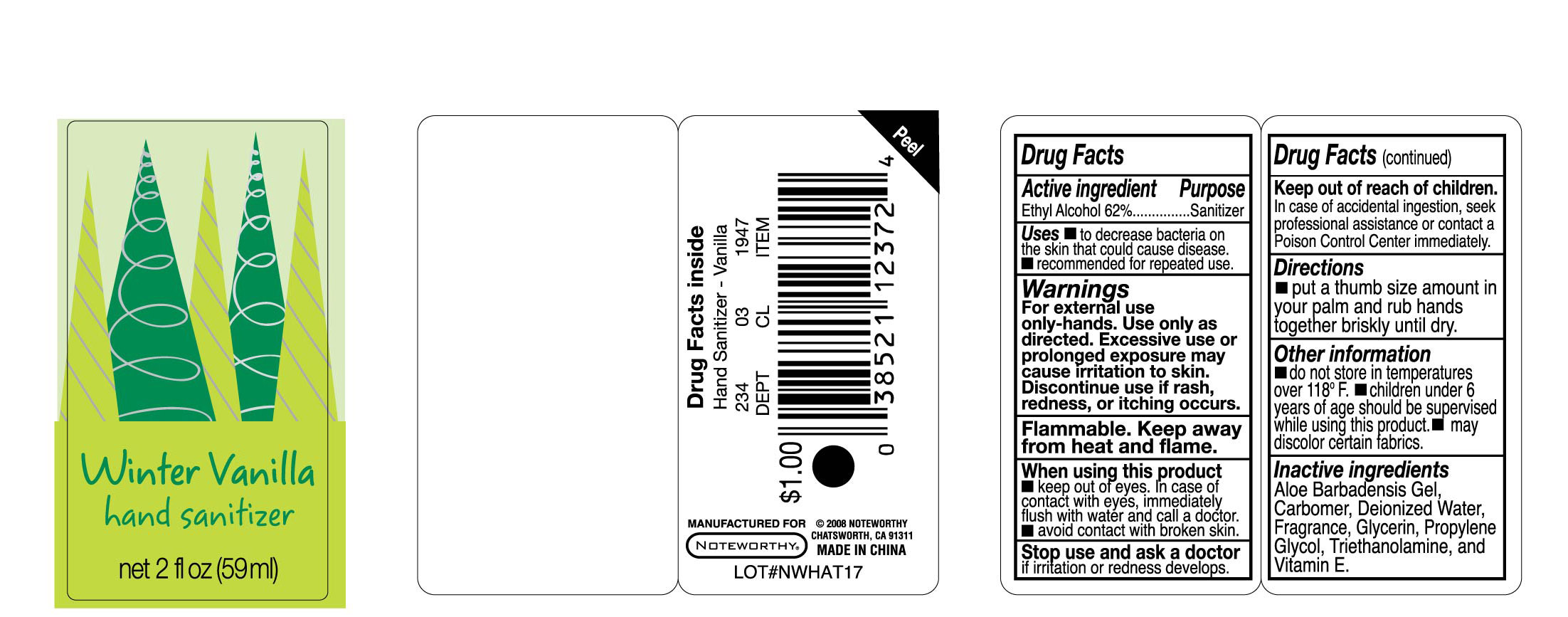 DRUG LABEL: Winter Vanilla Hand Sanitizer
NDC: 25225-011 | Form: LIQUID
Manufacturer: Unique Holding Group Inc
Category: otc | Type: HUMAN OTC DRUG LABEL
Date: 20091110

ACTIVE INGREDIENTS: ALCOHOL 62 g/100 g
INACTIVE INGREDIENTS: Propylene Glycol  0.5 g/100 g; Glycerin 1 g/100 g; ALOE VERA LEAF 0.01 g/100 g; CARBOMER HOMOPOLYMER TYPE C 0.33 g/100 g; Vitamin E 0.01 g/100 g; TROLAMINE 0.35 g/100 g; WATER 35.6 g/100 g

Drug Facts

DESCRIPTION

Put a thumb size amount in your palm and rub your hand briskly until dry.

STORAGE AND HANDLING

Do not store in temperatures over 118F children under six years of age should be supervise while using this product. May discolor certain fabrics.

INACTIVE INGREDIENT

Aloe Barbadensis Gel, Carbomer, Deionized water, Propylene glycol, Glycerin, Triethanolamine, Vitamin E, Fragance, may contain DC red 33, FDC blue 1

GERIATRIC USE

To decrease bacteria on the skin that could cause disease. Recommended for repeated use.

PACKAGE LABEL

labelpicture